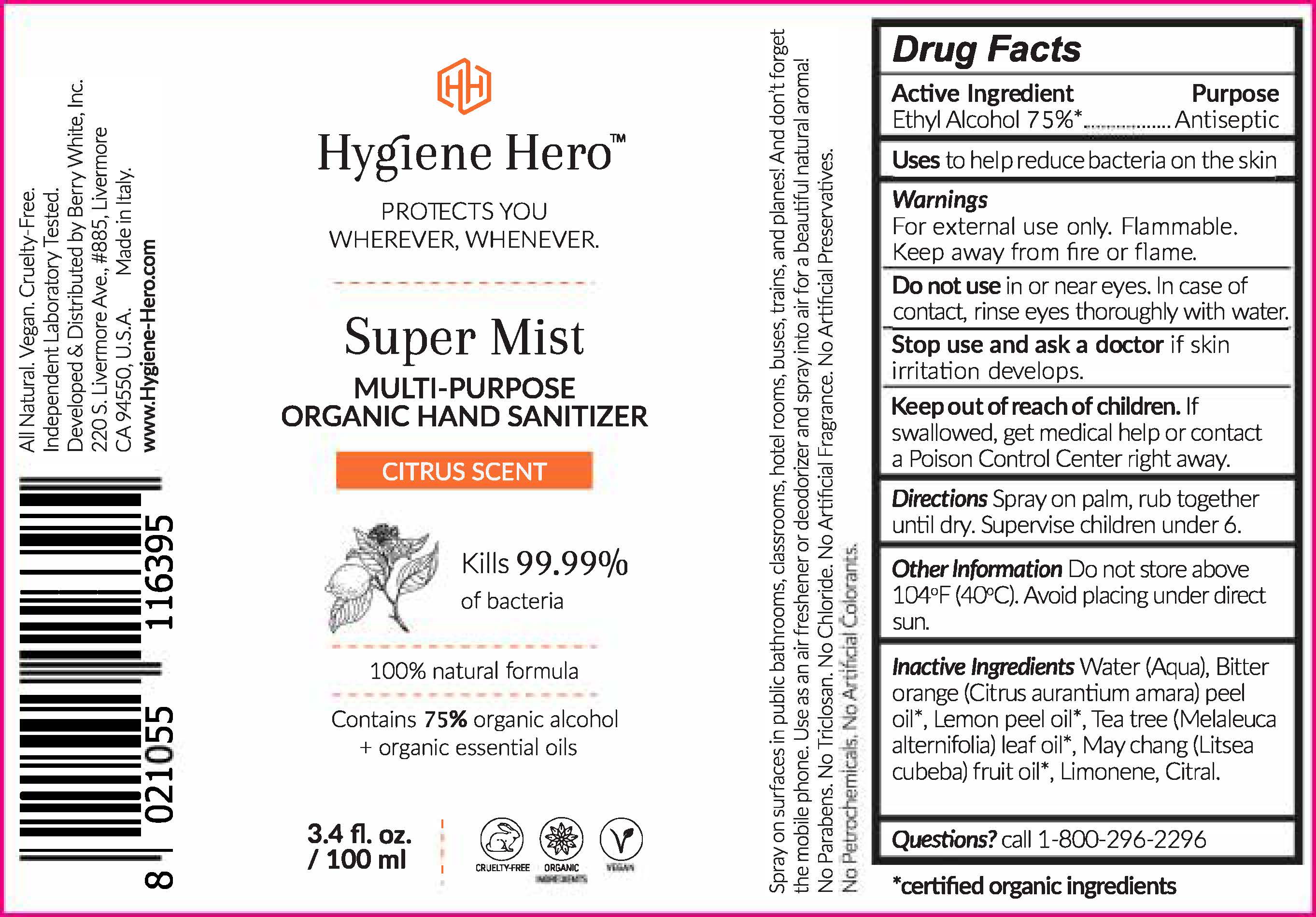 DRUG LABEL: Hygiene Hero
NDC: 74540-246 | Form: LIQUID
Manufacturer: Linea Bly SRL
Category: otc | Type: HUMAN OTC DRUG LABEL
Date: 20200423

ACTIVE INGREDIENTS: ALCOHOL 75 mL/100 mL
INACTIVE INGREDIENTS: CITRAL; TEA TREE OIL; LIMONENE, (+)-; LITSEA OIL; BITTER ORANGE OIL; LEMON OIL, TERPENELESS; WATER

Active Ingredient(s)

Alcohol 80% v/v. Purpose: Antiseptic

Purpose

Antiseptic, Hand Sanitizer

Use

to help reduce bacteria on the skin

Warnings

For external use only. Flammable. Keep away from heat or flame

Do not use

near eyes. In case of contact, rinse eyes thoroughly with water.

When using this product keep out of eyes, ears, and mouth. In case of contact with eyes, rinse eyes thoroughly with water.
Stop use and ask a doctor if irritation or rash occurs. These may be signs of a serious condition.
Keep out of reach of children. If swallowed, get medical help or contact a Poison Control Center right away.

Stop use and ask a doctor if irritation or rash occurs. These may be signs of a serious condition.

Keep out of reach of children. If swallowed, get medical help or contact a Poison Control Center right away.

Directions

Spray on palm, rub together until dry. Supervise children under 6.

Other information

Do not store above 104°F (40°C)。Avoid placing under direct sun.

Inactive ingredients

Water (Aqua), Bitter Orange (Citrus aurantium amara) peel oil*, Tea tree (Melaleuca Alternifolia) leaf oil*, May Chang (Litsea cubeba) fruit oil*, Limonene, Citral.